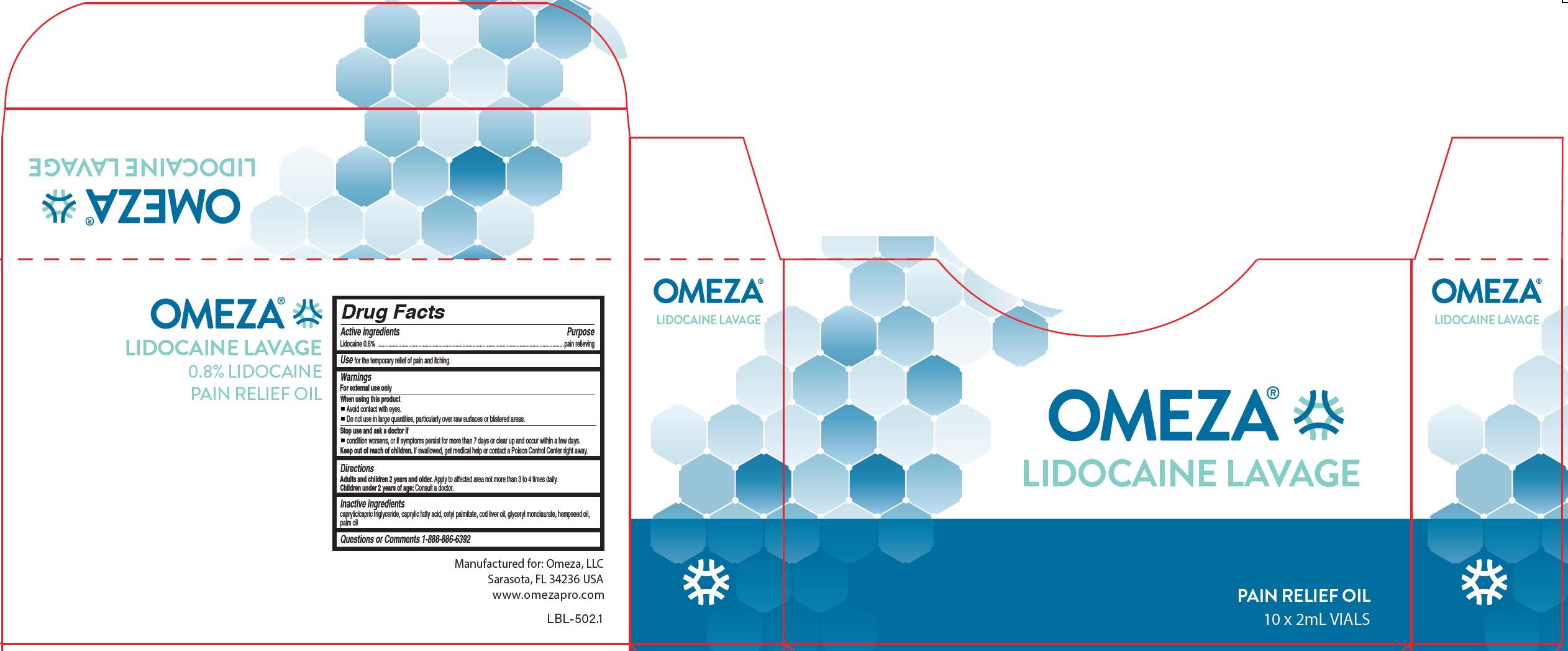 DRUG LABEL: Omeza Lidocaine Lavage
NDC: 73033-002 | Form: OIL
Manufacturer: Omeza LLC
Category: otc | Type: HUMAN OTC DRUG LABEL
Date: 20220922

ACTIVE INGREDIENTS: LIDOCAINE 8 mg/1 mL
INACTIVE INGREDIENTS: MEDIUM-CHAIN TRIGLYCERIDES; CETYL PALMITATE; COD LIVER OIL; GLYCERYL LAURATE; CANNABIS SATIVA SEED OIL; PALM OIL

Omeza Lidocaine Lavage

Active ingredients

Lidocaine 0.8%

Purpose

pain relieving

Use

for the temporary relief of pain and itching.

Warnings

For external use only

When using this product

- Avoid contact with eyes.

Do not use

- in large quantities, particularly over raw surfaces or blistered areas.

Stop use and ask a doctor if

- condition worsens, or if symptoms persist for more than 7 days or clear up and occur within a few days.

Keep out of reach of children.

If swallowed, get medical help or contact a Poison Control Center right away.

Directions

Adults and children 2 years and older. Apply to affected area not more than 3 to 4 times daily.
Children under 2 years of age: Consult a doctor.

Inactive ingredients

caprylic/capric triglyceride, caprylic fatty acid, cetyl palmitate, cod liver oil, glyceryl monolaurate, hempseed oil, palm oil

Questions or Comments

1-888-886-6392